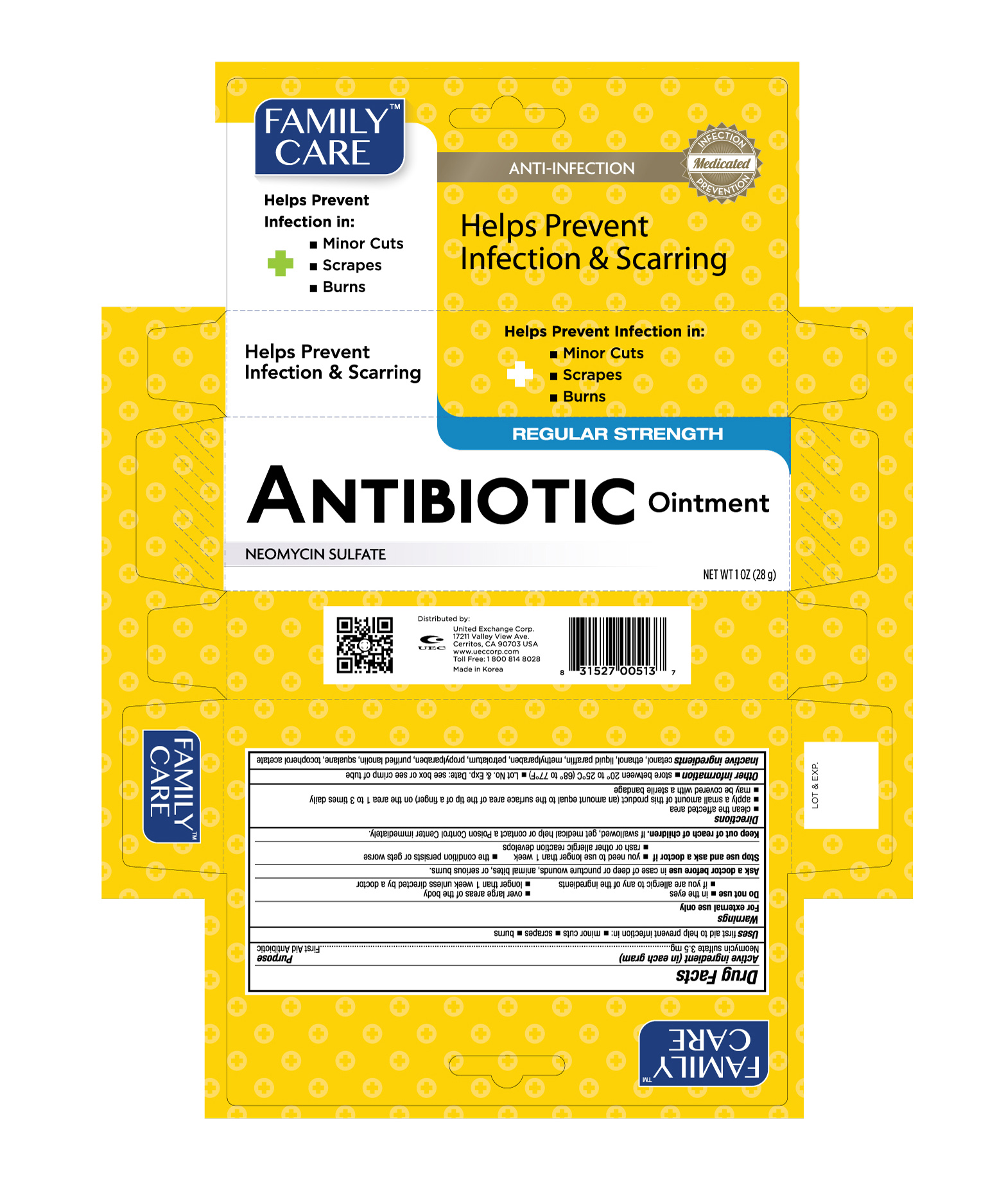 DRUG LABEL: Family Care Antibiotic
NDC: 65923-517 | Form: OINTMENT
Manufacturer: United Exchange Corp.
Category: otc | Type: HUMAN OTC DRUG LABEL
Date: 20171229

ACTIVE INGREDIENTS: NEOMYCIN SULFATE 3.5 mg/1 g
INACTIVE INGREDIENTS: PARAFFIN; PROPYLPARABEN; PETROLATUM; SQUALANE; METHYLPARABEN; LANOLIN; CETYL ALCOHOL; .ALPHA.-TOCOPHEROL ACETATE

Family Care Antibiotic Ointment 513

Active ingredient (in each gram) Purpose

Neomycin sulfate 3.5 mg...................................................................First Aid-Antibiotic

Warnings

For external use only

Uses

first aid to help prevent infection in:

- minor cuts
- scrapes
- burns

Do not use

- in the eyes
- if you are allergic to any of the ingredients
- over large areas of the body
- longer than 1 week unless directed by a doctor

Ask a doctor before use in case of deep or puncture wounds, animal bites, or serious burns

Stop use and ask a doctor if

- you need to use longer than 1 week
- rash or other allergic reaction develops
- the condition persists or gets worse

Keep out of reach of children. If swallowed, get medical help or contact a Poison Control Center immediately.

Directions

- clean the affected area
- apply a small amount of this product (an amount equal to the surface area of the tip of a finger) on the area 1 to 3 times daily
- may be covered with a sterile bandage

Other information

- store between 20° to 25°C (68° to 77°F)
- Lot No. & Exp. Date: see box or see crimp of tube

Inactive ingredients

cetanol, ethanol, liquid paraffin, methylparaben, petrolatum, propylparaben, purified lanolin, squalane, tocopherol acetate

DOSAGE AND ADMINISTRATION

Distributed by:

United Exchange Corp.

17211 Valley View Ave.

Cerritos, CA 90703 USA

www.ueccorp.com

1 800 814 8028

Made in Korea